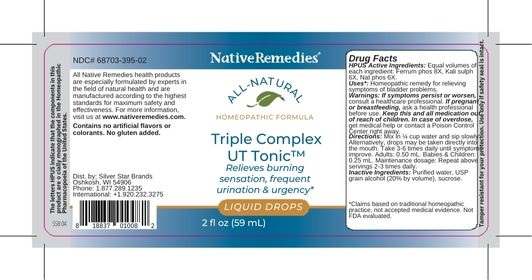 DRUG LABEL: NativeRemedies Triple Complex UT Tonic
NDC: 68703-395 | Form: LIQUID
Manufacturer: Silver Star Brands
Category: homeopathic | Type: HUMAN OTC DRUG LABEL
Date: 20250101

ACTIVE INGREDIENTS: POTASSIUM SULFATE 6 [hp_X]/59 mL; FERROSOFERRIC PHOSPHATE 8 [hp_X]/59 mL; SODIUM PHOSPHATE, DIBASIC 6 [hp_X]/59 mL
INACTIVE INGREDIENTS: ALCOHOL; WATER; SUCROSE

NativeRemedies® Triple Complex UT Tonic™

HPUS Active Ingredients: Equal volumes of each ingredient: Ferrum phos 8X, Kali sulph 6X, Nat phos 6X.

The letters HPUS indicate that the components in this product are officially monographed in the Homeopathic Pharmacopoeia of the United States.

Uses*

Uses*: Homeopathic remedy for relieving symptoms of bladder problems.

*Claims based on traditional homeopathic practice, not accepted medical evidence. Not FDA evaluated.

Warnings

Warnings: If symptoms persist or worsen, consult a healthcare professional. If pregnant or breastfeeding, ask a health professional before use. Keep this and all medication out of reach of children. In case of overdose, get medical help or contant a Poison Control Center right away.

Directions

Directions: Mix in 1/4 cup water and sip slowly. Alternatively, drops may be taken directly into the mouth. Take 3-6 times daily until symptoms improve. Adults: 0.50 mL. Babies & Children: 0.25 mL. Maintenance dosage: Repeat above servings 2-3 times daily.

OTHER SAFETY INFORMATION

Contains no artificial flavors or colorants. No gluten added.

Tamper resistant for your protection. Use only if safety seal is intact.

Inactive Ingredients

Inactive Ingredients: Purified water, USP grain alcohol (20% by volume), sucrose.

KEEP OUT OF REACH OF CHILDREN

Keep this and all medication out of reach of children. In case of overdose, get medical help or contact a Poison Control Center right away.

PREGNANCY OR BREAST FEEDING

If pregnant or breastfeeding, ask a health professional before use.

PURPOSE

Relieves burning sensation frequent urination & urgency.